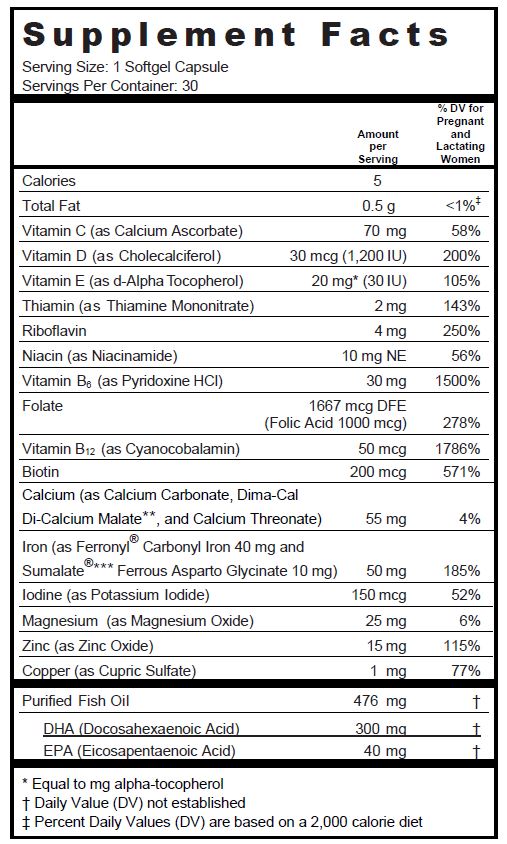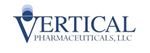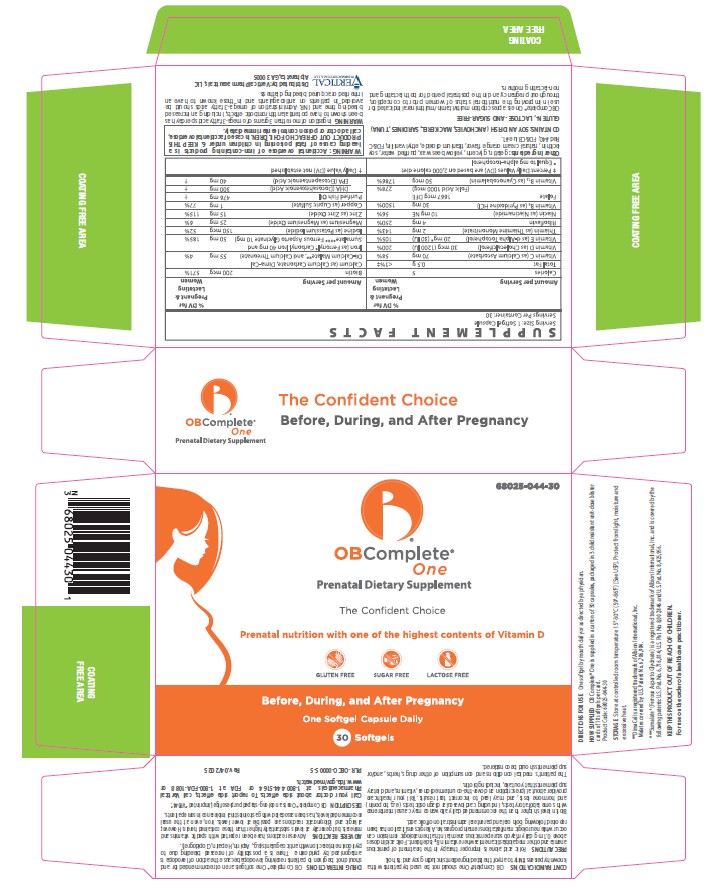 DRUG LABEL: OB Complete One
NDC: 68025-044 | Form: CAPSULE, LIQUID FILLED
Manufacturer: Vertical Pharmaceuticals, LLC
Category: other | Type: DIETARY SUPPLEMENT
Date: 20220218

ACTIVE INGREDIENTS: FISH OIL 476 mg/1 1; DOCONEXENT 300 mg/1 1; ICOSAPENT 40 mg/1 1; CALCIUM ASCORBATE 70 mg/1 1; CHOLECALCIFEROL 1200 [iU]/1 1; .ALPHA.-TOCOPHEROL ACETATE, D- 30 [iU]/1 1; THIAMINE MONONITRATE 2 mg/1 1; RIBOFLAVIN 4 mg/1 1; NIACINAMIDE 10 mg/1 1; PYRIDOXINE HYDROCHLORIDE 30 mg/1 1; FOLIC ACID 1 mg/1 1; CYANOCOBALAMIN 50 ug/1 1; BIOTIN 200 ug/1 1; CALCIUM THREONATE 5 mg/1 1; CALCIUM MALATE 25 mg/1 1; CALCIUM CARBONATE 25 mg/1 1; IRON 40 mg/1 1; FERROUS ASPARTO GLYCINATE 10 mg/1 1; POTASSIUM IODIDE 150 ug/1 1; MAGNESIUM OXIDE 25 mg/1 1; ZINC OXIDE 15 mg/1 1; CUPRIC SULFATE 1 mg/1 1
INACTIVE INGREDIENTS: YELLOW WAX; LECITHIN, SOYBEAN; GELATIN; GLYCERIN; WATER; ORANGE OIL; TITANIUM DIOXIDE; FD&C RED NO. 40; ETHYL VANILLIN; FD&C BLUE NO. 1

OB Complete® One

SUPPLEMENT FACTS

Other Ingredients: gelatin, glycerin, yellow bees wax, purified water, soy lecithin, natural cream orange flavor, titanium dioxide, ethyl vanillin, FD&C Red #40, FD&C Blue #1.

CONTAINS: SOY AND FISH (ANCHOVIES, MACKEREL, SARDINES, TUNA)

GLUTEN-, LACTOSE- AND SUGAR-FREE

OB Complete® One is a prescription multivitamin/multimineral indicated for use in improving the nutritional status of women prior to conception, throughout pregnancy, and in the postnatal period for both lactating and non-lactating mothers.

CONTRAINDICATIONS

OB Complete® One should not be used by patients with a known hypersensitivity to any of the listed ingredients including soy and fish oil.

WARNINGS

WARNING: Accidental overdose of iron-containing products is a leading cause of fatal poisoning in children under 6. KEEP THIS PRODUCT OUT OF REACH OF CHILDREN. In case of accidental overdose, call a doctor or poison control center immediately.

PRECAUTIONS

Folic acid alone is improper therapy in the treatment of pernicious anemia and other megaloblastic anemias where vitamin B12 is deficient. Folic acid in doses above 0.1 mg daily may obscure pernicious anemia in that hematologic remission can occur while neurologic manifestations remain progressive. Allergic sensitization has been reported following both oral and parenteral administration of folic acid.

Biotin levels higher than the recommended daily allowance may cause interference with some laboratory tests, including cardiovascular diagnostic tests (e.g. troponin) and hormone tests, and may lead to incorrect test results. Tell your healthcare provider about all prescription and over-the-counter medicines, vitamins, and dietary supplements that you take, including biotin.

The patient’s medical conditions and consumption of other drugs, herbs, and/or supplements should be considered.

DRUG INTERACTIONS

OB Complete® One softgels are not recommended for and should not be given to patients receiving levodopa because the action of levodopa is antagonized by pyridoxine. There is a possibility of increased bleeding due to pyridoxine interaction with anticoagulants (e.g., Aspirin, Heparin, Clopidogrel).

ADVERSE REACTIONS

Adverse reactions have been reported with specific vitamins and minerals but generally at levels substantially higher than those contained herein. However, allergic and idiosyncratic reactions are possible at lower levels. Iron, even at the usual recommended levels, has been associated with gastrointestinal intolerance in some patients.

DESCRIPTION

OB Complete® One is an oblong-shaped purple softgel, imprinted "VP044".

DIRECTIONS FOR USE

One softgel by mouth daily or as directed by a physician.

HOW SUPPLIED

OB Complete® One is supplied in a carton of 30 capsules, packaged in 3 child resistant unit-dose blister cards of 10 softgels per card.

Product Code: 68025-044-30

STORAGE

Store at controlled room temperature 15°-30°C (59°-86°F) [See USP]. Protect from light, moisture and excessive heat.

HEALTH CLAIM

KEEP THIS PRODUCT OUT OF REACH OF CHILDREN.

*DimaCal is a registered trademark of Albion International, Inc.

Malates covered by U.S. Patent No. 6,706,904.

**Sumalate® (Ferrous Asparto Glycinate) is a registered trademark of Albion International, Inc. and is covered by the following patents: U.S. Pat. No. 6,716,814; U.S. Pat. No. 8,007,846 and U.S. Pat. No. 8,425,956.

For use on the order of a healthcare practitioner.

Call your doctor about side effects. To report side effects, call Vertical Pharmaceuticals at 1-770-509-4500 or FDA at 1-800-FDA-1088 or www.fda.gov/medwatch.

PLR-OBCO-00005-5 Rev. 04/2025

Distributed by:

Vertical Pharmaceuticals, LLC

Alpharetta, GA 30005

PRINCIPAL DISPLAY PANEL

68025-044-30

OB
COMPLETE®
One

Gluten,
Lactose and
Sugar-Free

VERTICAL
PHARMACEUTICALS, LLC

30 Softgels